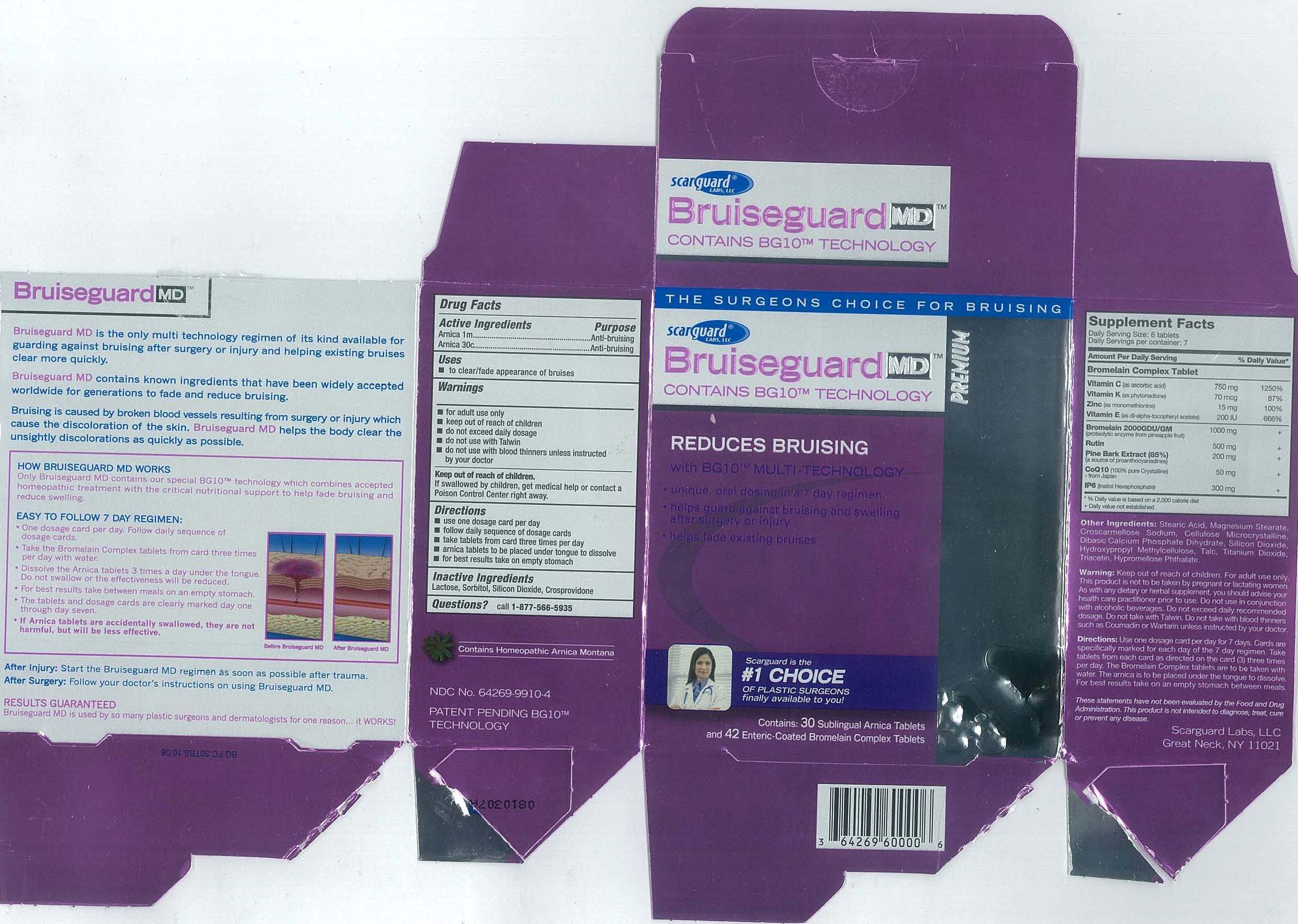 DRUG LABEL: Bruiseguard MD
NDC: 64269-9910 | Form: KIT | Route: SUBLINGUAL
Manufacturer: Scarguard Labs, LLC
Category: homeopathic | Type: HUMAN OTC DRUG LABEL
Date: 20091222

ACTIVE INGREDIENTS: ARNICA MONTANA 1 [hp_M]/1 1; ARNICA MONTANA 30 [hp_C]/1 1
INACTIVE INGREDIENTS: SORBITOL; SILICON DIOXIDE; LACTOSE; CROSPOVIDONE; SORBITOL; SILICON DIOXIDE; LACTOSE; CROSPOVIDONE

DRUG FACTS

Active Ingredients

Arnica 1m
Arnica 30c

Purpose

Anti-bruising

Anti-bruising

Uses

to clear/fade appearance of bruises

Warnings

- for adult use only
- keep out of reach of children
- do not exceed daily dosage
- do not use with Talwin
- do not use with blood thinners unless instructed by your doctor

Keep out of reach of children

If swallowed by children, get medical help or contact a Poison Control Center right away.

Directions

- use one dosage card per day
- follow daily sequence of dosage cards
- take tablets from card three times per day
- arnica tablets to be placed under tongue to dissolve
- for best results take on empty stomach

Inactive ingredients

Lactose, Sorbitol, Silicone Dioxide, Crospovidone

QUESTIONS

call 1-877-566-5935